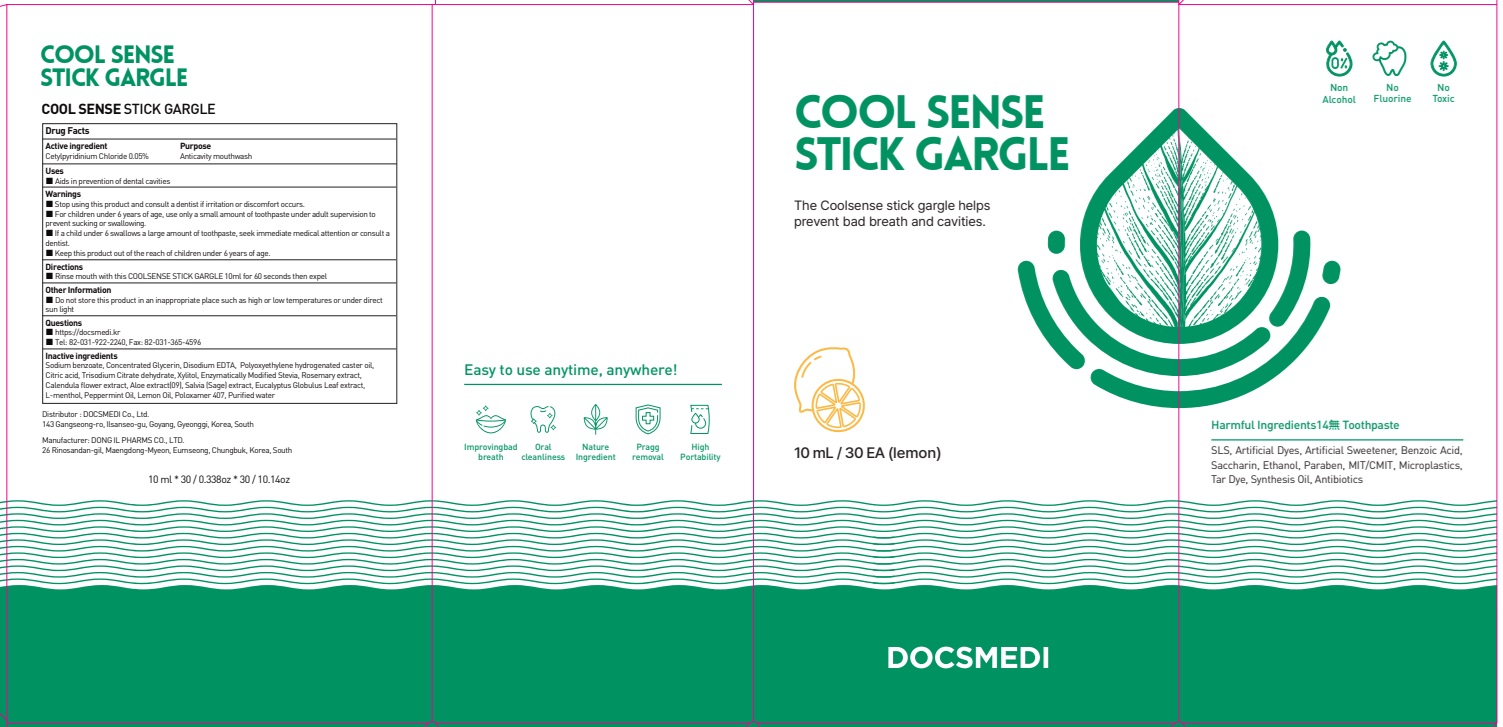 DRUG LABEL: COOL SENSE STICK GARGLE
NDC: 76670-0015 | Form: LIQUID
Manufacturer: DOCSMEDI Co., Ltd.
Category: otc | Type: HUMAN OTC DRUG LABEL
Date: 20250122

ACTIVE INGREDIENTS: CETYLPYRIDINIUM CHLORIDE 0.05 g/100 mL
INACTIVE INGREDIENTS: SODIUM BENZOATE; GLYCERIN

ACTIVE INGREDIENT

Cetylpyridinium Chloride 0.05%

Inactive ingredients

Sodium benzoate, Concentrated Glycerin, Disodium EDTA, Polyoxyethylene hydrogenated caster oil, Citric acid, Trisodium Citrate dehydrate, Xylitol, Enzymatically Modified Stevia, Rosemary extract, Calendula flower extract, Aloe extract(09), Salvia (Sage) extract, Eucalyptus Globulus Leaf extract, L-menthol, Peppermint Oil, Lemon Oil, Poloxamer 407, Purified water

PURPOSE

Anticavity mouthwash

WARNINGS

■ Stop using this product and consult a dentist if irritation or discomfort occurs.

■ For children under 6 years of age, use only a small amount of toothpaste under adult supervision to prevent sucking or swallowing.

■ If a child under 6 swallows a large amount of toothpaste, seek immediate medical attention or consult a dentist.

■ Keep this product out of the reach of children under 6 years of age

KEEP OUT OF REACH OF CHILDREN

■ Keep this product out of the reach of children under 6 years of age.

Uses

■ Aids in prevention of dental cavities

Directions

■ Rinse mouth with this COOLSENSE STICK GARGLE 10ml for 60 seconds then expel

Other Information

■ Do not store this product in an inappropriate place such as high or low temperatures or under direct sun light

Questions

■ https://docsmedi.kr

■ Tel: 82-031-922-2240, Fax: 82-031-365-4596